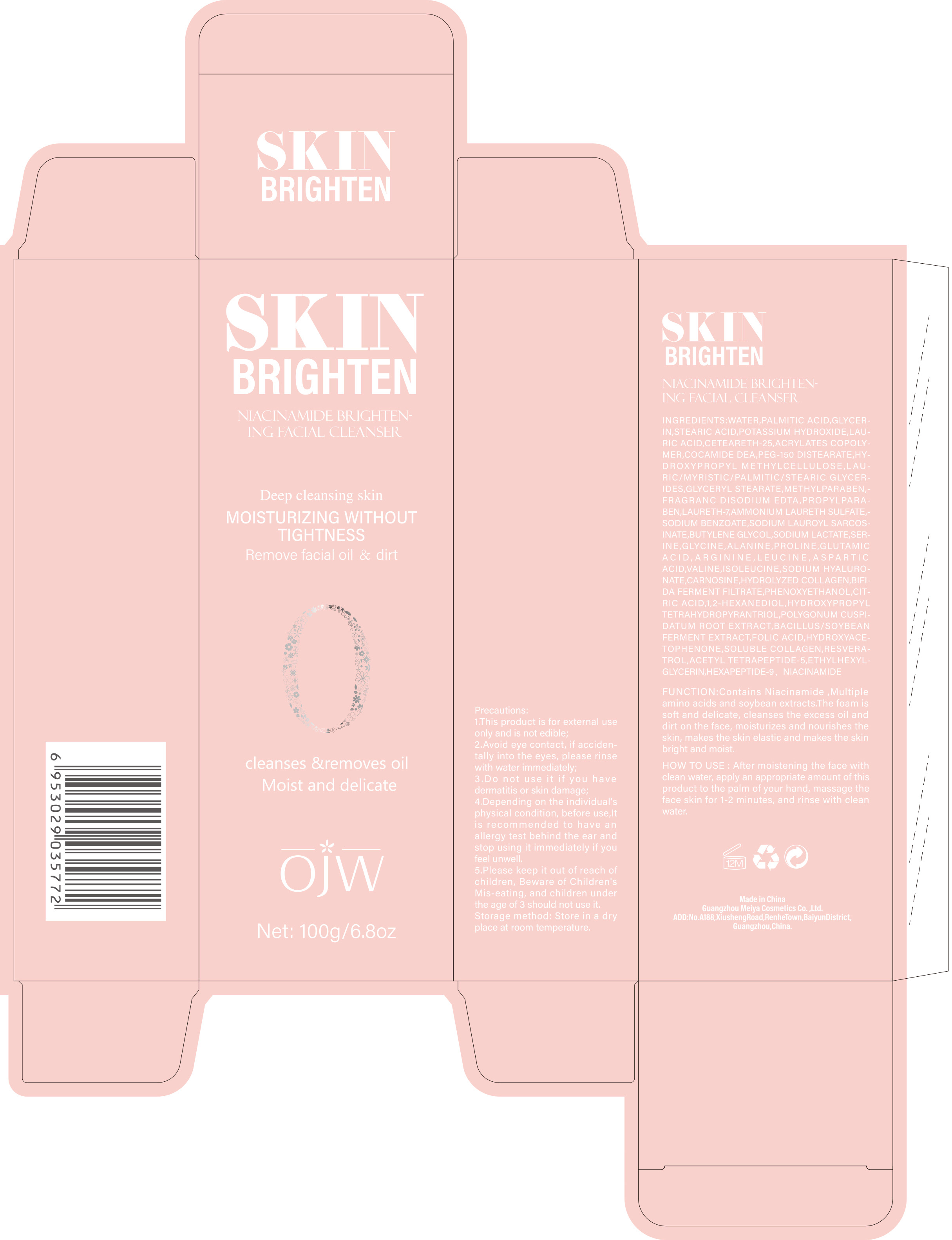 DRUG LABEL: Niacinamide Brightening Facial Cleanser
NDC: 84673-006 | Form: EMULSION
Manufacturer: Guangzhou Meiya Cosmetics Co., Ltd.
Category: otc | Type: HUMAN OTC DRUG LABEL
Date: 20240917

ACTIVE INGREDIENTS: NIACINAMIDE 1 g/1 mg; RESVERATROL 1 g/1 mg
INACTIVE INGREDIENTS: LAURIC ACID 4 g/1 mg; ALANINE 1 g/1 mg; GLUTAMIC ACID 1 g/1 mg; VALINE 1 g/1 mg; HYDROXYPROPYL TETRAHYDROPYRANTRIOL 1 g/1 mg; SODIUM LAUROYL SARCOSINATE 1 g/1 mg; POTASSIUM HYDROXIDE 1 g/1 mg; GLYCINE 1 g/1 mg; HEXAPEPTIDE-9 1 g/1 mg; SERINE 1 g/1 mg; ASPARTIC ACID 1 g/1 mg; 1,2-HEXANEDIOL 1 g/1 mg; PHENOXYETHANOL 1 g/1 mg; SODIUM BENZOATE 0.17 g/1 mg; METHYLPARABEN 0.2 g/1 mg; STEARIC ACID 1 g/1 mg; PALMITIC ACID 1.38 g/1 mg; PEG-150 DISTEARATE 0.5 g/1 mg; FOLIC ACID 1 g/1 mg; SODIUM LACTATE 1 g/1 mg; HYDROXYACETOPHENONE 1 g/1 mg; ETHYLHEXYLGLYCERIN 1 g/1 mg; ACETYL TETRAPEPTIDE-5 1 g/1 mg; CETEARETH-25 1 g/1 mg; PROLINE 1 g/1 mg; CARNOSINE 1 g/1 mg; LAURETH-7 0.07 g/1 mg; PROPYLPARABEN 0.1 g/1 mg; WATER 46.769 g/1 mg; LEUCINE 1 g/1 mg; GLYCERIN 0.1 g/1 mg; ISOLEUCINE 1 g/1 mg; ARGININE 1 g/1 mg

ACTIVE INGREDIENT

NIACINAMIDE 2%

RESVERATROL 0.3%

PURPOSE

Function:Contains Niacinamide ,Multiple amino acids and soybean extracts.The foam is soft and delicate, cleanses the excess oil and dirt on the face, moisturizes and nourishes the skin, makes the skin elastic and makes the skin bright and moist.

INDICATIONS AND USAGE

HOW TO USE : After moistening the face with clean water, apply an appropriate amount of this product to the palm of your hand, massage the face skin for 1-2 minutes, and rinse with clean water.

WARNINGS

1. This product is for external use only and is not edible;

2. Avoid eye contact, if accidentally into the eyes, please rinse with water immediately;

3. Do not use it if you have dermatitis or skin damage;

4. Depending on the individual's physical condition, before use,It is recommended to have an allergy test behind the ear and stop using it immediately if you feel unwell.

5. Please keep it out of reach of children, Beware of Children's Mis-eating, and children under the age of 3 should not use it.

STOP USE

1. Avoid eye contact, if accidentally into the eyes, please rinse with water immediately;

2. Do not use it if you have dermatitis or skin damage;

3. Depending on the individual's physical condition, before use,It is recommended to have an allergy test behind the ear and stop using it immediately if you feel unwell.

DO NOT USE

1. This product is for external use only and is not edible;

2. Avoid eye contact, if accidentally into the eyes, please rinse with water immediately;

3. Do not use it if you have dermatitis or skin damage;

4. Depending on the individual's physical condition, before use,It is recommended to have an allergy test behind the ear and stop using it immediately if you feel unwell.

KEEP OUT OF REACH OF CHILDREN

Please keep it out of reach of children, Beware of Children's Mis-eating, and children under the age of 3 should not use it.

WHEN USING

Avoid eye contact, if accidentally into the eyes, please rinse with water immediately;

DOSAGE AND ADMINISTRATION

After moistening the face with clean water, apply an appropriate amount of this product to the palm of your hand, massage the face skin for 1-2 minutes, and rinse with clean water.